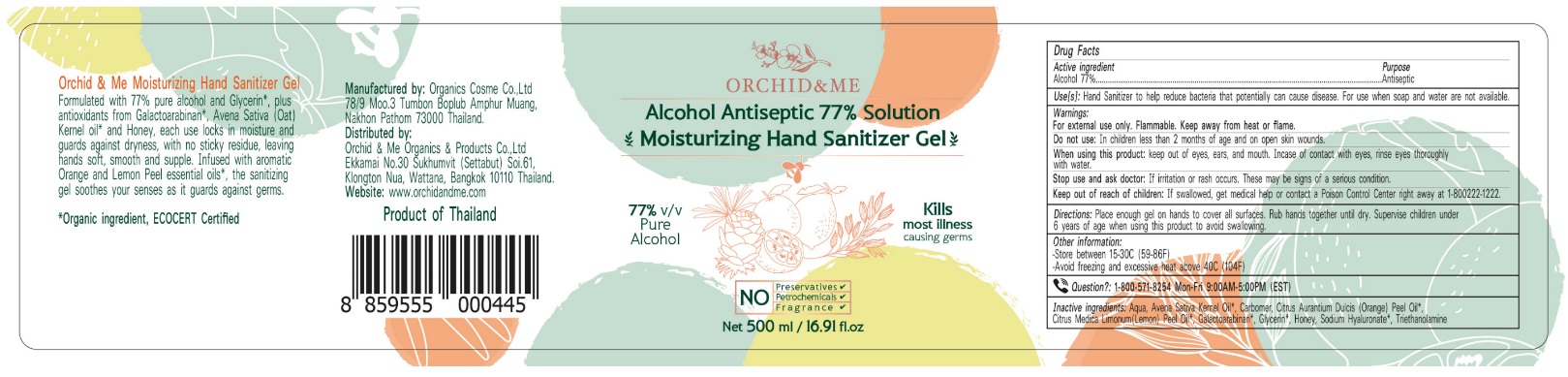 DRUG LABEL: Orchid and Me Moisturizing Hand Sanitizer
NDC: 90018-002 | Form: GEL
Manufacturer: ORCHID & ME ORGANICS & PRODUCTS COMPANY LIMITED
Category: otc | Type: HUMAN OTC DRUG LABEL
Date: 20201027

ACTIVE INGREDIENTS: ALCOHOL 77 mL/100 mL
INACTIVE INGREDIENTS: WATER; GLYCERIN; HONEY; GALACTOARABINAN; TROLAMINE; ORANGE OIL; LEMON OIL; CARBOMER HOMOPOLYMER, UNSPECIFIED TYPE; OAT KERNEL OIL; HYALURONATE SODIUM

Active Ingredient

Alcohol 77% v/v.

Purpose

Antiseptic

Use

Hand Sanitizer to help reduce bacteria that potentially can cause disease. For use when soap and water are not available.

Warnings

For external use only. Flammable. Keep away from heat or flame

Do not use

in children less than 2 months of age and on open skin wounds

When using this product keep out of eyes, ears, and mouth. In case of contact with eyes, rinse eyes thoroughly with water.

Stop use and ask a doctor if irritation or rash occurs. These may be signs of a serious condition.

Keep out of reach of children. If swallowed, get medical help or contact a Poison Control Center right away at 1-800222-1222.

Directions

- Place enough product on hands to cover all surfaces. Rub hands together until dry.
- Supervise children under 6 years of age when using this product to avoid swallowing.

Other information

- Store between 15-30C (59-86F)
- Avoid freezing and excessive heat above 40C (104F)

Questions?

1-800-571-8254 Mon-Fri 9:00 AM- 5:00 PM (EST)

Inactive ingredients

Aqua, Avena sativa Kernel Oil, Carbomer, Citrus Aurantium Dulcis (Orange) Peel Oil, Citrus Medica Limonum (Lemon) Peel Oil, Galactoarabinan, Glycerin, Honey, Sodium Hyaluronate, Triethanolamine